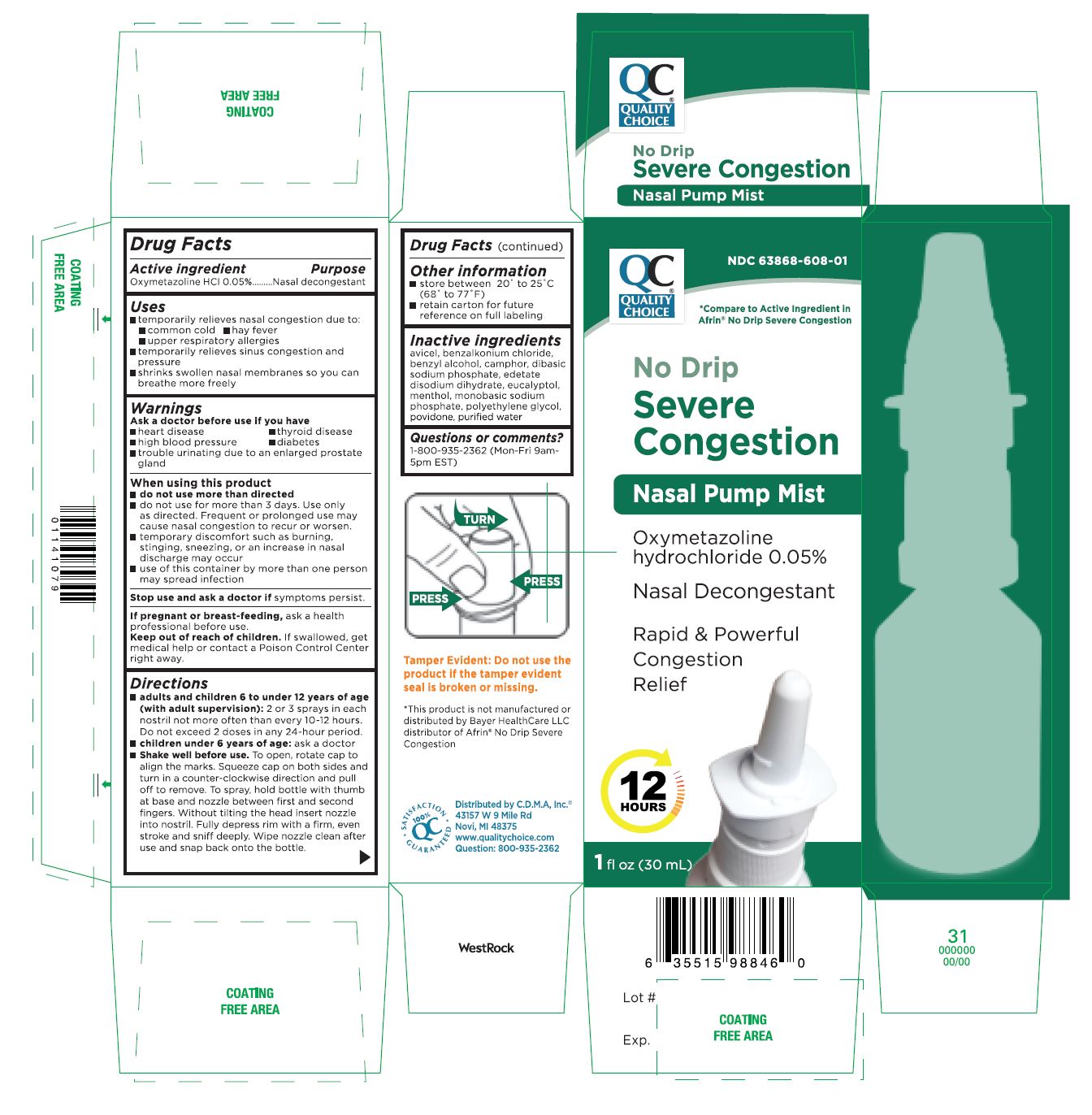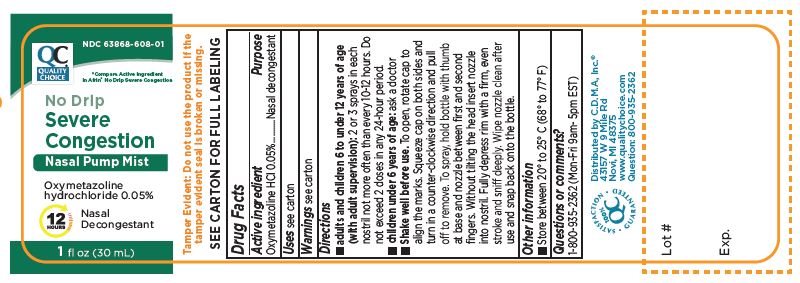 DRUG LABEL: OXYMETAZOLINE HYDROCHLORIDE
NDC: 63868-608 | Form: SOLUTION
Manufacturer: CHAIN DRUG MARKETING ASSOCIATION INC
Category: otc | Type: HUMAN OTC DRUG LABEL
Date: 20241226

ACTIVE INGREDIENTS: OXYMETAZOLINE HYDROCHLORIDE 0.05 mg/1 mL
INACTIVE INGREDIENTS: BENZALKONIUM CHLORIDE; MICROCRYSTALLINE CELLULOSE; BENZYL ALCOHOL; CAMPHOR (NATURAL); SODIUM PHOSPHATE DIBASIC DIHYDRATE; EDETATE DISODIUM; EUCALYPTOL; MENTHOL; WATER; SODIUM PHOSPHATE, MONOBASIC; POLYETHYLENE GLYCOL, UNSPECIFIED; POVIDONE

No Drip Severe Congestion
Nasal Pump Mist

Active Ingredient Purpose

Oxymetazoline HCI 0.05% ....... Nasal decongestant

PURPOSE

- Rapid & Powerful Congestion Relief

Uses

- temporarily relieves nasal congestion due to:
  - common cold
  - hay fever
  - upper respiratory allergies
- temporarily relieves sinus congestion and pressure
- shrinks swollen nasal membranes so you can breathe more freely

Warnings

Warnings Ask a doctor before use if you have

- heart disease
- thyroid disease
- high blood pressure
- diabetes
- trouble urinating due to an enlarged prostate gland

When using this product

- do not use more than directed
- do not use for more than 3 days. Use only as directed. Frequent or prolonged use may cause nasal congestion to recur or worsen.
- temporary discomfort such as burning, stinging, sneezing, or an increase in nasal discharge may occur
- use of this container by more than one person may spread infection

Stop use and ask a doctor if symptoms persist.

PREGNANCY OR BREAST FEEDING

If pregnant or breast feeding, ask a health professional before use.

Keep out of reach of children. If swallowed, get medical help or contact a Poison Control Center right away.

Directions

- adults and children 6 to under 12 years of age (with adult supervision): 2 or 3 sprays in each nostril not more often than every 10-12 hours. Do not exceed 2 doses in any 24-hour period.
- children under 6 years of age: ask a doctor
- Shake well before use. To open, rotate cap to align the marks. Squeeze cap on both sides and turn in a counter-clockwise direction and pull off to remove. To spray, hold bottle with thumb at base and nozzle between first and second fingers. Without tilting the head insert nozzle into nostril. Fully depress rim with a firm, even stroke and sniff deeply. Wipe nozzle clean after use and snap back onto the bottle.

Other information

- store between 20° -25°C (68°-77 °F)
- retain carton for future reference on full labeling

Questions or comments?
1-800-935-2362 (Mon-Fri 9am-5pm EST)

Inactive ingredients

avicel, benzalkonium chloride, benzyl alcohol, camphor, dibasic sodium phosphate, edetate disodium dihydrate, eucalyptol, menthol, monobasic sodium phosphate, polyethylene glycol, povidone, purified water

*This product is not manufactured or distributed by Bayer HealthCare LLC mdistributor of Afrin No Drip Severe Congestion

Distributed by C.D.M.A. lnc.
43157 W 9 Mile Rd
Novi, MI 48375
www.qualitychoice.com
Question: 800-935-2362